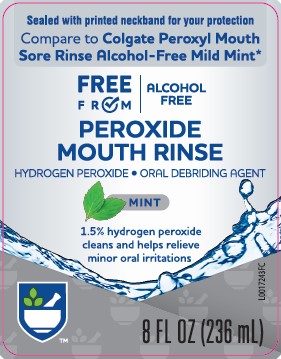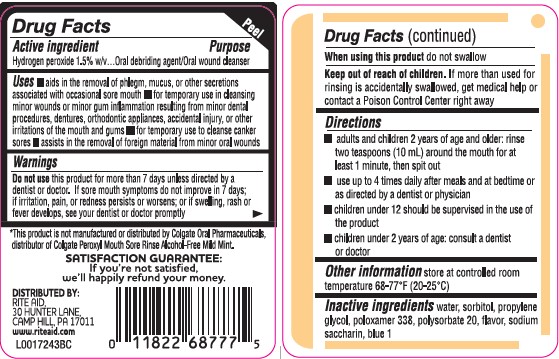 DRUG LABEL: Sore Mouth Cleanser
NDC: 11822-1462 | Form: MOUTHWASH
Manufacturer: Rite Aid Corporation
Category: otc | Type: HUMAN OTC DRUG LABEL
Date: 20260130

ACTIVE INGREDIENTS: HYDROGEN PEROXIDE 1588 mg/1 mL
INACTIVE INGREDIENTS: WATER; SORBITOL; PROPYLENE GLYCOL; POLOXAMER 338; POLYSORBATE 20; SACCHARIN SODIUM; FD&C BLUE NO. 1

Rite Aid 462.002/462AA rev 1
Alcohol-Free Mint Peroxide Rinse

Active ingredient

Hydrogen peroxide 15% w/v

Purpose

Oral debriding agent/Oral wound cleanser

Uses

- aids in the removal of phlgem, mucus, or other secretions associated with occasional sore mouth
- for temporary use in cleansing minor wounds or minor gum inflammation resulting from minor dental procedures, dentures, orthodontic appliances, acidental injury, or other irritations of the mouth and gums
- for temporary use to cleanse canker sores
- assists in the removal of foreign material from minor oral wounds

Warnings

For this product

Do not use

this product for more than 7 days unless directed by a dentist or doctor. If sore mouth symptoms do not improve in 7 days: if irritation, pain, or redness persists or worsens; or if swelling, rash or fever develops, see your dentist or doctor promptly

When using this product

do not swallow

Keep out of reach of children.

If more than used for rinsing is accidentally swallowed, get medical help or contact a Poison Control Center right away.

Directions

- adults and children 2 years of age and older: rinse two teaspoons (10 mL) around the mouth for at least 1 minute, then spit out
- use up to 4 times daily after meals and at bedtime or as directed by a dentist or physician
- children under 12 should be supervised in the use of the product
- children under 2 years of age: consult a dentist or doctor

other information

store at controlled room temperature 68-77°F (20-25°C)

Inactive ingredients

water, sorbitol, propylene glycol, poloxamer 338, polysorbate 20, flavor, sodium saccharin, blue 1

Disclaimer

*This product is not manufactured or distributed by Colgate Oral Pharmaceuticals, distributor of Colgate Peroxyl Mouth Sore Rinse Alcohol-Free Mild Mint.

Adverse Reactions

SATISFACTION GUARANTEE:

If you're not satisfied, we'll happily refund your money.

DISTRIBUTED BY:

RITE AID

30 HUNTER LANE

CAMP HILL, PA 17011

www.riteaid.com

principal display panel

Sealed with printed neckband for your protection

Compare to Colgate Peroxyl Mouth Sore Rinse Alcohol-Free Mild Mint*

FREE FROM ALCOHOL FREE

PEROXIDE MOUTH RINSE

HYDROGEN PEROXIDE • ORAL DEBRIDING AGENT

MINT

1.5% hydrogen peroxide cleans and helps relieve minor irritations

8 FL OZ (236 mL)